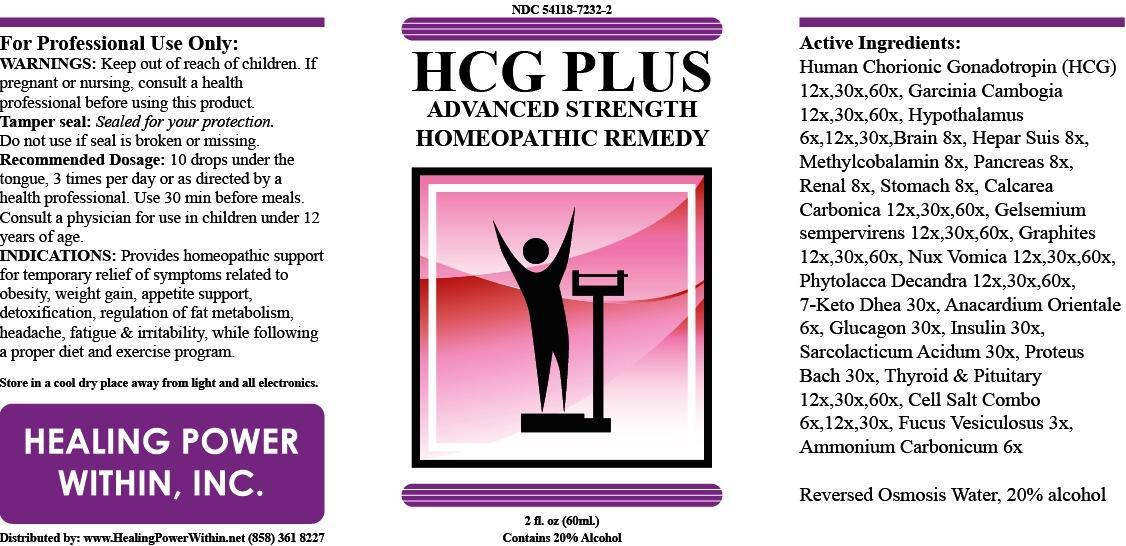 DRUG LABEL: HCG Plus
NDC: 54118-7232 | Form: SOLUTION/ DROPS
Manufacturer: ABCO Laboratories, Inc.
Category: homeopathic | Type: HUMAN OTC DRUG LABEL
Date: 20140405

ACTIVE INGREDIENTS: GONADOTROPHIN, CHORIONIC 12 [hp_X]/60 mL; GARCINIA CAMBOGIA FRUIT 12 [hp_X]/60 mL; BOS TAURUS HYPOTHALAMUS 6 [hp_X]/60 mL; BOS TAURUS BRAIN 8 [hp_X]/60 mL; PORK LIVER 8 [hp_X]/60 mL; METHYLCOBALAMIN 8 [hp_X]/60 mL; SUS SCROFA PANCREAS 8 [hp_X]/60 mL; BEEF KIDNEY 8 [hp_X]/60 mL; TRIPE 8 [hp_X]/60 mL; CALCIUM CARBONATE 12 [hp_X]/60 mL; GELSEMIUM SEMPERVIRENS WHOLE 12 [hp_X]/60 mL; GRAPHITE 12 [hp_X]/60 mL; STRYCHNOS NUX-VOMICA SEED 12 [hp_X]/60 mL; PHYTOLACCA AMERICANA ROOT 12 [hp_X]/60 mL; 7-KETO-DEHYDROEPIANDROSTERONE 30 [hp_X]/60 mL; SEMECARPUS ANACARDIUM JUICE 6 [hp_X]/60 mL; GLUCAGON 30 [hp_X]/60 mL; INSULIN HUMAN 30 [hp_X]/60 mL; LACTIC ACID, L- 30 [hp_X]/60 mL; PROTEUS INCONSTANS 30 [hp_X]/60 mL; THYROID, UNSPECIFIED 12 [hp_X]/60 mL; BOS TAURUS PITUITARY GLAND 12 [hp_X]/60 mL; CALCIUM FLUORIDE 6 [hp_X]/60 mL; FUCUS VESICULOSUS 3 [hp_X]/60 mL; AMMONIUM CARBONATE 6 [hp_X]/60 mL
INACTIVE INGREDIENTS: WATER; ALCOHOL

HCG Plus

ACTIVE INGREDIENT

- Human Chorionic Gonadotropin (HCG) 12x, 30x, 60x
- Garcinia Cambogia 12x, 30x, 60x
- Hypothalamus 6x, 12x, 30x
- Brain 8x
- Hepar Suis 8x
- Methylcobalamin 8x
- Pancreas 8x
- Renal 8x
- Stomach 8x
- Calcarea carbonica 12x, 30x, 60x
- Gelsemium sempervirens 12x, 30x, 60x
- Graphites 12x, 30x, 60x
- Nux Vomica 12x, 30x, 60x
- Phytolacca Decandra 12x, 30x, 60x
- 7-Keto DHEA 30x
- Anacardium Orientale 6x
- Glucagon 30x
- Insulin 30x
- Sarcolacticum Acidum 30x
- Proteus Bach 30x
- Thyroid 12x, 30x, 60x
- Pituitary 12x, 30x, 60x
- Cell salt combo 6x, 12x, 30x
- Fucus Vesiculosus 3x
- Ammonium carbonicum 6x

PURPOSE

- Provides homeopathic support for temporary relief of symptioms related to obesity, weight gain, appetite support, detoxification, regulation of fat metabolism, headache,
- fatigue and irritability, while following a proper diet and exercise program.

- Keep out of reach of children

INDICATIONS AND USAGE

- Provides homeopathic support for temporary relief of symptioms related to obesity, weight gain, appetite support, detoxification, regulation of fat metabolism, headache,
- fatigue and irritability, while following a proper diet and exercise program.

- Keep out of reach of children.
- If pregnant or nursing, consult a health professional before using this product
- Tamper seal: Sealed for your protedtion. Do not use if seal is broken or missing.

DOSAGE AND ADMINISTRATION

- 10 drops under the tongue, 3 times per day or as directed by a health professional.
- Use 30 min. before meals.
- Consult a physician for use in children under 12 years of age.

INACTIVE INGREDIENT

- Reversed Osmosis Water
- 20% alcohol

- image of label
- hcgpluslabel.jpg